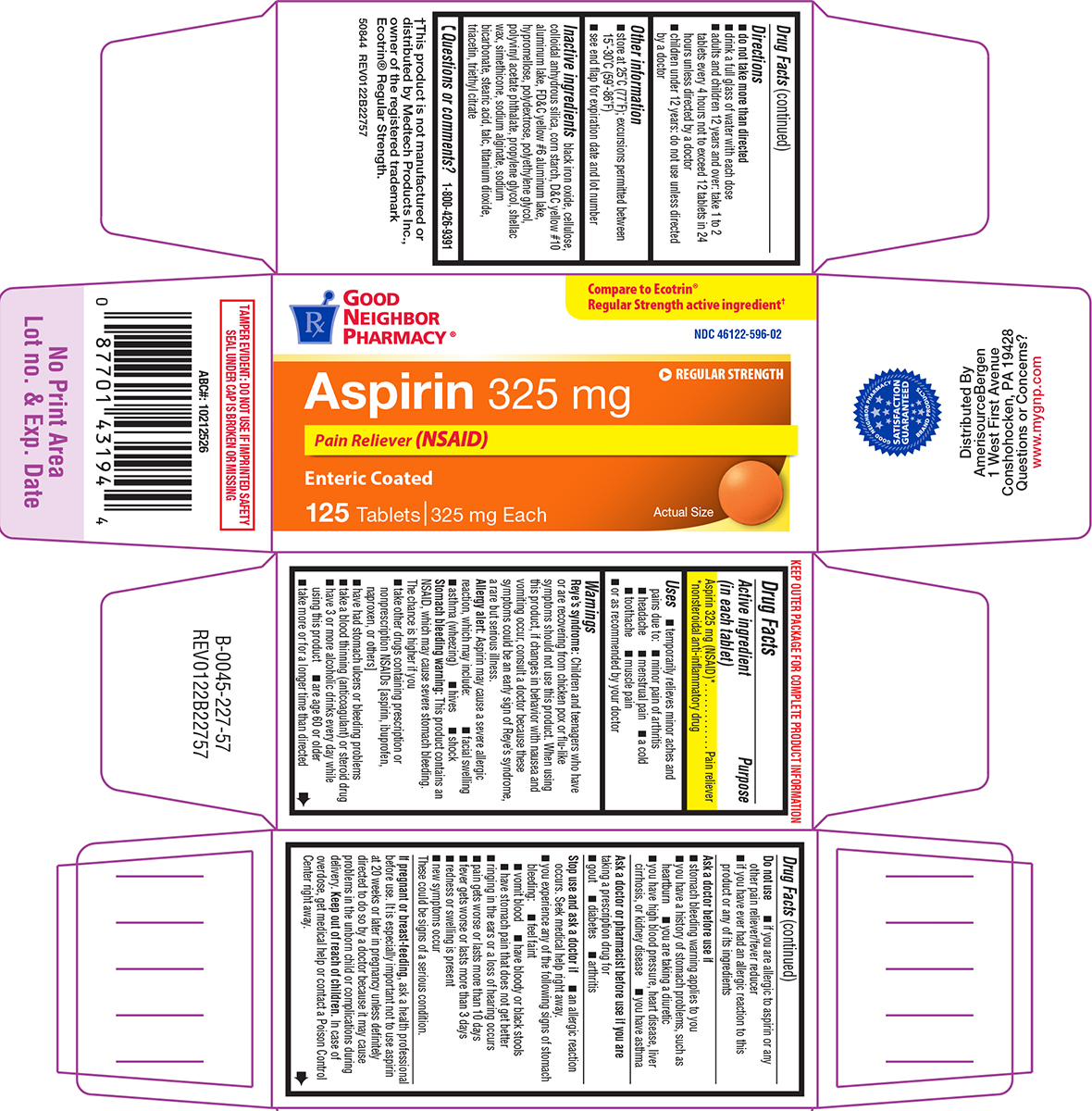 DRUG LABEL: Aspirin
NDC: 46122-596 | Form: TABLET, DELAYED RELEASE
Manufacturer: Amerisource Bergen
Category: otc | Type: HUMAN OTC DRUG LABEL
Date: 20260107

ACTIVE INGREDIENTS: ASPIRIN 325 mg/1 1
INACTIVE INGREDIENTS: FERROSOFERRIC OXIDE; POWDERED CELLULOSE; SILICON DIOXIDE; STARCH, CORN; D&C YELLOW NO. 10 ALUMINUM LAKE; FD&C YELLOW NO. 6 ALUMINUM LAKE; HYPROMELLOSE, UNSPECIFIED; POLYDEXTROSE; POLYETHYLENE GLYCOL, UNSPECIFIED; Polyvinyl Acetate Phthalate; PROPYLENE GLYCOL; SHELLAC; DIMETHICONE; WATER; SODIUM ALGINATE; SODIUM BICARBONATE; STEARIC ACID; TALC; TITANIUM DIOXIDE; TRIACETIN; TRIETHYL CITRATE

Good Neighbor Pharmacy 44-227

Active ingredient (in each tablet)

Aspirin 325 mg (NSAID)*
*nonsteroidal anti-inflammatory drug

Purpose

Pain reliever

Uses

- temporarily relieves minor aches and pains due to:
  - minor pain of arthritis
  - headache
  - menstrual pain
  - a cold
  - toothache
  - muscle pain
- or as recommended by your doctor

Warnings

Reye’s syndrome: Children and teenagers who have or are recovering from chicken pox or flu-like symptoms should not use this product. When using this product, if changes in behavior with nausea and vomiting occur, consult a doctor because these symptoms could be an early sign of Reye's syndrome, a rare but serious illness.

Allergy alert: Aspirin may cause a severe allergic reaction, which may include:

- facial swelling
- asthma (wheezing)
- hives
- shock

Stomach bleeding warning: This product contains an NSAID, which may cause severe stomach bleeding. The chance is higher if you

- take other drugs containing prescription or nonprescription NSAIDs [aspirin, ibuprofen, naproxen, or others]
- have had stomach ulcers or bleeding problems
- take a blood thinning (anticoagulant) or steroid drug
- have 3 or more alcoholic drinks every day while using this product
- are age 60 or older
- take more or for a longer time than directed

Do not use

- if you are allergic to aspirin or any other pain reliever/fever reducer
- if you have ever had an allergic reaction to this product or any of its ingredients

Ask a doctor before use if

- stomach bleeding warning applies to you
- you have a history of stomach problems, such as heartburn
- you are taking a diuretic
- you have high blood pressure, heart disease, liver cirrhosis, or kidney disease
- you have asthma

Ask a doctor or pharmacist before use if you are

taking a prescription drug for

- gout
- diabetes
- arthritis

Stop use and ask a doctor if

- an allergic reaction occurs. Seek medical help right away.
- you experience any of the following signs of stomach bleeding:
  - feel faint
  - vomit blood
  - have bloody or black stools
  - have stomach pain that does not get better
- ringing in the ears or a loss of hearing occurs
- pain gets worse or lasts more than 10 days
- fever gets worse or lasts more than 3 days
- redness or swelling is present
- new symptoms occur

These could be signs of a serious condition.

If pregnant or breast-feeding,

ask a health professional before use. It is especially important not to use aspirin at 20 weeks or later in pregnancy unless definitely directed to do so by a doctor because it may cause problems in the unborn child or complications during delivery.

Keep out of reach of children.

In case of overdose, get medical help or contact a Poison Control Center right away.

Directions

- do not take more than directed
- drink a full glass of water with each dose
- adults and children 12 years and over: take 1 to 2 tablets every 4 hours not to exceed 12 tablets in 24 hours unless directed by a doctor
- children under 12 years: do not use unless directed by a doctor

Other information

- store at 25°C (77°F); excursions permitted between 15°-30°C (59°-86°F)
- see end flap for expiration date and lot number

Inactive ingredients

black iron oxide, cellulose, colloidal anhydrous silica, corn starch, D&C yellow #10 aluminum lake, FD&C yellow #6 aluminum lake, hypromellose, polydextrose, polyethylene glycol, polyvinyl acetate phthalate, propylene glycol, shellac wax, simethicone, sodium alginate, sodium bicarbonate, stearic acid, talc, titanium dioxide, triacetin, triethyl citrate

Questions or comments?

1-800-426-9391

Principal display panel

GOOD
NEIGHBOR
PHARMACY®

Compare to Ecotrin®
Regular Strength active ingredient†

NDC 46122-596-02

REGULAR STRENGTH

Aspirin 325 mg
Pain Reliever (NSAID)

Enteric Coated

125 Tablets | 325 mg Each

Actual Size

†This product is not manufactured or
distributed by Medtech Products Inc.,
owner of the registered trademark
Ecotrin® Regular Strength.
50844 REV0122B22757

TAMPER EVIDENT: DO NOT USE IF IMPRINTED
SAFETY SEAL UNDER CAP IS BROKEN OR MISSING

Distributed By
AmerisourceBergen
1 West First Avenue
Conshohocken, PA 19428
Questions or Concerns?
www.mygnp.com

GOOD NEIGHBOR PHARMACY
BRAND PRODUCTS

SATISFACTION GUARANTEED

Good Neighbor Pharmacy 44-227